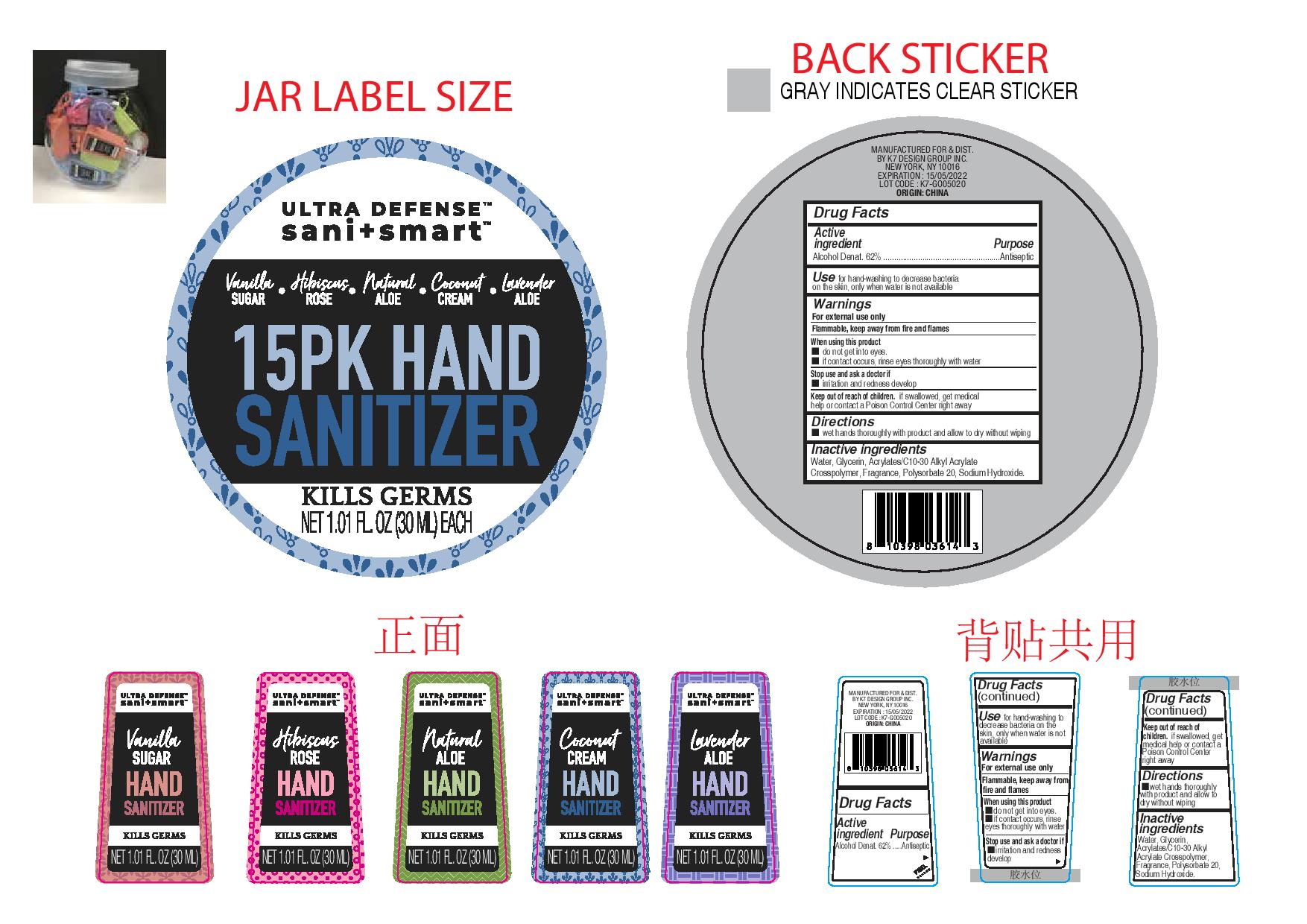 DRUG LABEL: Ultra Defense Sani Smart 15 PK Hand Sanitizer
NDC: 51522-005 | Form: GEL
Manufacturer: Gold Orient International Limited
Category: otc | Type: HUMAN OTC DRUG LABEL
Date: 20200427

ACTIVE INGREDIENTS: ALCOHOL 65 mL/100 mL
INACTIVE INGREDIENTS: CARBOMER INTERPOLYMER TYPE A (55000 CPS); POLYSORBATE 20; SODIUM HYDROXIDE; GLYCERIN; WATER

Active Ingredient(s)

Alcohol Denat. 62%

Purpose

Antiseptic, Hand Sanitizer

Use

Hand Sanitizer to decrease bacteria on the skin, only when water is not available.

Warnings

For external use only. Flammable. Keep away from heat or flame

WHEN USING

- do not get into eyes
- if contact occurs, rinse eyes thoroughly with water

Stop use and ask a doctor if irritation or rash occurs.

Keep out of reach of children. If swallowed, get medical help or contact a Poison Control Center right away.

Directions

- Wet hands thorough;y with product and allow to dry without wiping

Other information

- Store between 15-30C (59-86F)
- Avoid freezing and excessive heat above 40C (104F)

Inactive ingredients

glycerin, water, Acrylates/C10-30 Alkyl Acrylate Crosspolymer, Fragrance, Polysorbate 20, Sodium Hydroxide